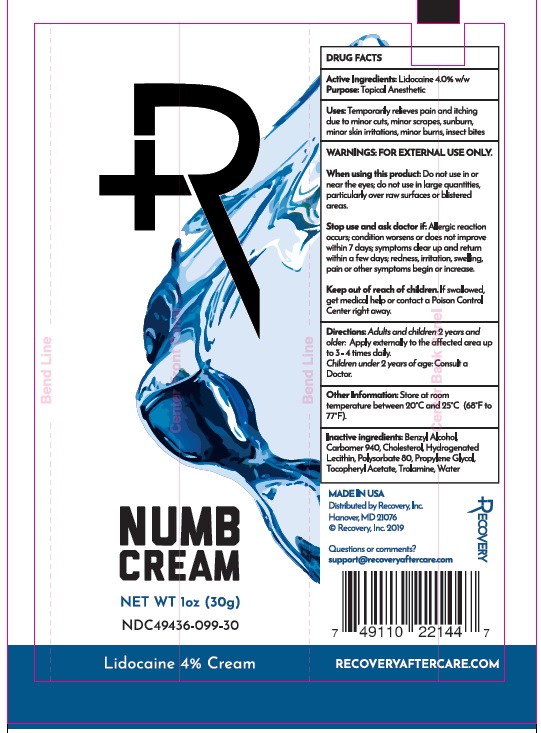 DRUG LABEL: Recovery Numb
NDC: 49436-099 | Form: CREAM
Manufacturer: PURKLENZ FORMULATIONS INC.
Category: otc | Type: HUMAN OTC DRUG LABEL
Date: 20251112

ACTIVE INGREDIENTS: LIDOCAINE 4 g/100 g
INACTIVE INGREDIENTS: BENZYL ALCOHOL; CARBOMER 940; CHOLESTEROL; LECITHIN, SOYBEAN; POLYSORBATE 80; PROPYLENE GLYCOL; .ALPHA.-TOCOPHEROL ACETATE, DL-; TROLAMINE; WATER

Recovery Numb Cream

DRUG FACTS

Active Ingredients: Lidocaine 4% w/w

Purpose: Topical Anesthetic

INDICATIONS AND USAGE

Uses: Temporarily relieves pain and itching
due to minor cuts, minor scrapes, sunburn,
minor skin irritations, minor burns, insect bites.

WARNINGS: FOR EXTERNAL USE ONLY.

When using this product: Do not use in or
near the eyes; do not use in large quantities;
particularly over raw surfaces or blistered areas.

Stop use and ask doctor if: Allergic reaction
occurs; condition worsens or does not improve
within 7 days; symptoms clear up and return
within a few days; redness, irritation, swelling,
pain or other symptoms begin or increase.

Keep out of reach of children: If swallowed,
get medical help or contact a Poison Control
Center right away

DOSAGE AND ADMINISTRATION

Directions: Adults and children 2 years and
older: Apply externally to the affected area up
to 3-4 times daily.
Children under 2 years of age: Consult a
doctor.

Other Information: Store at room
temperature 20°C and 25°C (68°F to
77°F).

Inactive ingredients: Benzyl Alcohol,
Carbomer 940, Cholesterol, Hydrogenated
Lecithin, Polysorbate 80, Propylene Glycol,
Tocopherol Acetate, Trolamine, Water

Package Label

NUMB

CREAM

NET WT 1 oz (30g)

NDC 49426-099-30

Lidocaine 4% Cream

RECOVERYAFTERCARE.COM

Made in USA

Distributed by Recovery, Inc.

Hanover, MD 21076

© Recovery, Inc. 2019

Questions or comments?

support@recoveryaftercare.com

RECOVERY

7 49110 22144 7

res